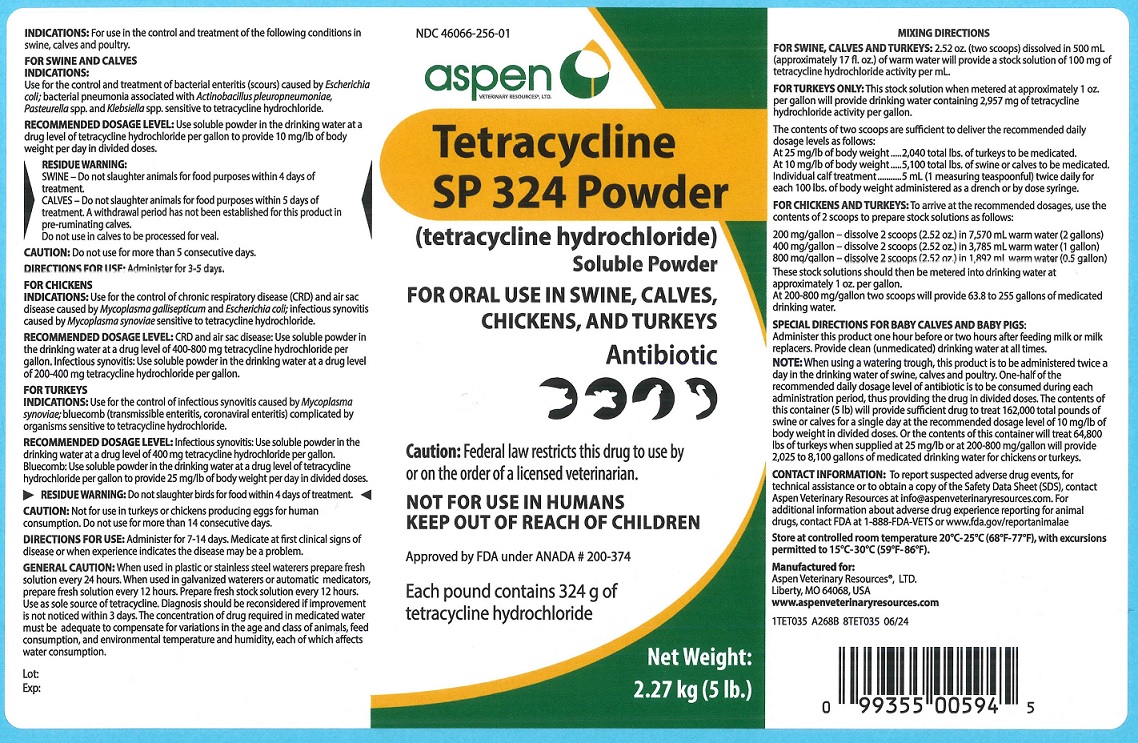 DRUG LABEL: Tetracycline
NDC: 46066-256 | Form: POWDER
Manufacturer: Aspen Veterinary Resources
Category: animal | Type: PRESCRIPTION ANIMAL DRUG LABEL
Date: 20250820

ACTIVE INGREDIENTS: TETRACYCLINE 324 g/2.27 kg

DESCRIPTION

Tetracycline SP 324 Powder
(tetracycline hydrochloride)
Soluble Powder

FOR ORAL USE IN SWINE, CALVES, CHICKENS, AND TURKEYS

Antibiotic

CAUTION: Federal law restricts this drug to use by or on the order of a licensed veterinarian.

NOT FOR USE IN HUMANS
KEEP OUT OF REACH OF CHILDREN

Approved by FDA under ANADA # 200-374

Each pound contains 324 g of tetracycline hydrochloride.

Net Weight: 2.27 kg (5 lb.)

INDICATIONS AND USAGE

INDICATIONS: For use in the control and treatment of the following conditions in swine, calves and poultry.

FOR SWINE AND CALVES
INDICATIONS: Use for the control and treatment of bacterial enteritis (scours) caused by Escherichia coli; bacterial pneumonia associated with Actinobacillus pleuropneumoniae, Pasteurella spp., and Klebsiella spp. sensitive to tetracycline hydrochloride.
RECOMMENDED DOSAGE LEVEL: Use soluble powder in the drinking water at a drug level of tetracycline hydrochloride per gallon to provide 10 mg/lb of body weight per day in divided doses.
RESIDUE WARNING: SWINE – Do not slaughter animals for food purposes within 4 days of treatment.
CALVES – Do not slaughter animals for food purposes within 5 days of treatment. A withdrawal period has not been established for this product in pre-ruminating calves.
Do not use in calves to be processed for veal.
CAUTION: Do not use for more than 5 consecutive days.
DIRECTIONS FOR USE: Administer for 3-5 days.

FOR CHICKENS
INDICATIONS: Use for the control of chronic respiratory disease (CRD) and air sac disease caused by Mycoplasma gallisepticum and Escherichia coli; infectious synovitis caused by Mycoplasma synoviae sensitive to tetracycline hydrochloride.

RECOMMENDED DOSAGE LEVEL: CRD and air sac disease: Use soluble powder in the drinking water at a drug level of 400-800 mg tetracycline hydrochloride per gallon. Infectious synovitis: Use soluble powder in the drinking water at a drug level of 200-400 mg tetracycline hydrochloride per gallon.

FOR TURKEYS
INDICATIONS: Use for the control of infectious synovitis caused by Mycoplasma synoviae; bluecomb (transmissible enteritis, coronaviral enteritis) complicated by organisms sensitive to tetracycline hydrochloride.
RECOMMENDED DOSAGE LEVEL: Infectious synovitis: Use soluble powder in the drinking water at a drug level of 400 mg tetracycline hydrochloride per gallon. Bluecomb: Use soluble powder in the drinking water at a drug level of tetracycline hydrochloride per gallon to provide 25 mg/lb of body weight per day in divided doses.
RESIDUE WARNING: Do not slaughter birds for food within 4 days of treatment.
CAUTION: Not for use in turkeys or chickens producing eggs for human consumption.
Do not use for more than 14 consecutive days.
DIRECTIONS FOR USE: Administer for 7-14 days. Medicate at first clinical signs of disease or when experience dictates the disease may be a problem.

GENERAL PRECAUTIONS

GENERAL CAUTION: When used in plastic or stainless steel waterers prepare fresh solution every 24 hours. When used in galvanized waterers or automatic medicators, prepare fresh solution every 12 hours. Prepare fresh stock solution every 12 hours. Use as sole source of tetracycline. Diagnosis should be reconsidered if improvement is not noticed within 3 days. The concentration of drug required in medicated water must be adequate to compensate for variations in the age and class of animals, feed consumption, and environmental temperature and humidity, each of which affects water consumption.

DOSAGE AND ADMINISTRATION

MIXING DIRECTIONS:
FOR SWINE, CALVES, AND TURKEYS: 2.52 oz. (two scoops) dissolved in 500 mL (approximately 17 fl. oz.) of warm water will provide a stock solution of 100 mg of tetracycline hydrochloride activity per mL.
FOR TURKEYS ONLY: This stock solution when metered at approximately 1 oz. per gallon will provide drinking water containing 2,957 mg of tetracycline hydrochloride activity per gallon.
The contents of two scoops are sufficient to deliver the recommended daily dosage levels as follows:
At 25 mg/lb of body weight 2,040 total lbs. of turkeys to be medicated.
At 10 mg/lb body weight 5,100 total lbs. of swine or calves to be medicated.
Individual calf treatment 5 mL (1 measuring teaspoonful) twice daily for each 100 lbs. of body weight administered as a drench or by dose syringe.

FOR CHICKENS AND TURKEYS: To arrive at the recommended dosages, use the contents of 2 scoops to prepare stock solutions as follows:
200 mg/gallon – dissolve 2 scoops (2.52 oz.) in 7,570 mL warm water (2 gallons)
400 mg/gallon – dissolve 2 scoops (2.52 oz.) in 3,785 mL warm water (1 gallon)
800 mg/gallon – dissolve 2 scoops (2.52 oz.) in 1,892 mL warm water (0.5 gallon)
These stock solutions should then be metered into drinking water at approximately 1 oz. per gallon.
At 200-800 mg/gallon two scoops will provide 63.8 to 255 gallons of medicated drinking water.

SPECIAL DIRECTIONS FOR BABY CALVES AND BABY PIGS:
Administer this product one hour before or two hours after feeding milk or milk replacers. Provide clean (unmedicated) drinking water at all times.
NOTE: When using a watering trough, this product is to be administered twice a day in the drinking water of swine, calves and poultry. One-half of the recommended daily dosage level of antibiotic is to be consumed during each administration period, thus providing the drug in divided doses. The contents of this container (5 lb) will provide sufficient drug to treat 162,000 total pounds of swine or calves for a single day at the recommended dosage level of 10 mg/lb of body weight in divided doses. Or the contents of this container will treat 64,800 lbs of turkeys when supplied at 25 mg/lb or at 200-800 mg/gallon will provide 2,025 to 8,100 gallons of medicated drinking water for chickens or turkeys.

CONTACT INFORMATION: To report suspected adverse drug events, for technical assistance or to obtain a copy of the Safety Data Sheet (SDS), contact Aspen Veterinary Resources at info@aspenveterinaryresources.com. For additional information about adverse drug experience reporting for animal drugs, contact FDA at 1-888-FDA-VETS or www.fda.gov/reportanimalae

STORAGE AND HANDLING

Store at controlled room temperature 20°C – 25°C (68°F-77°F), with excursions permitted to 15°C-30°C (59°F-86°F).

Manufactured for:
Aspen Veterinary Resources®, LTD.
Liberty, MO 64068, USA
www.aspenveterinaryresources.com